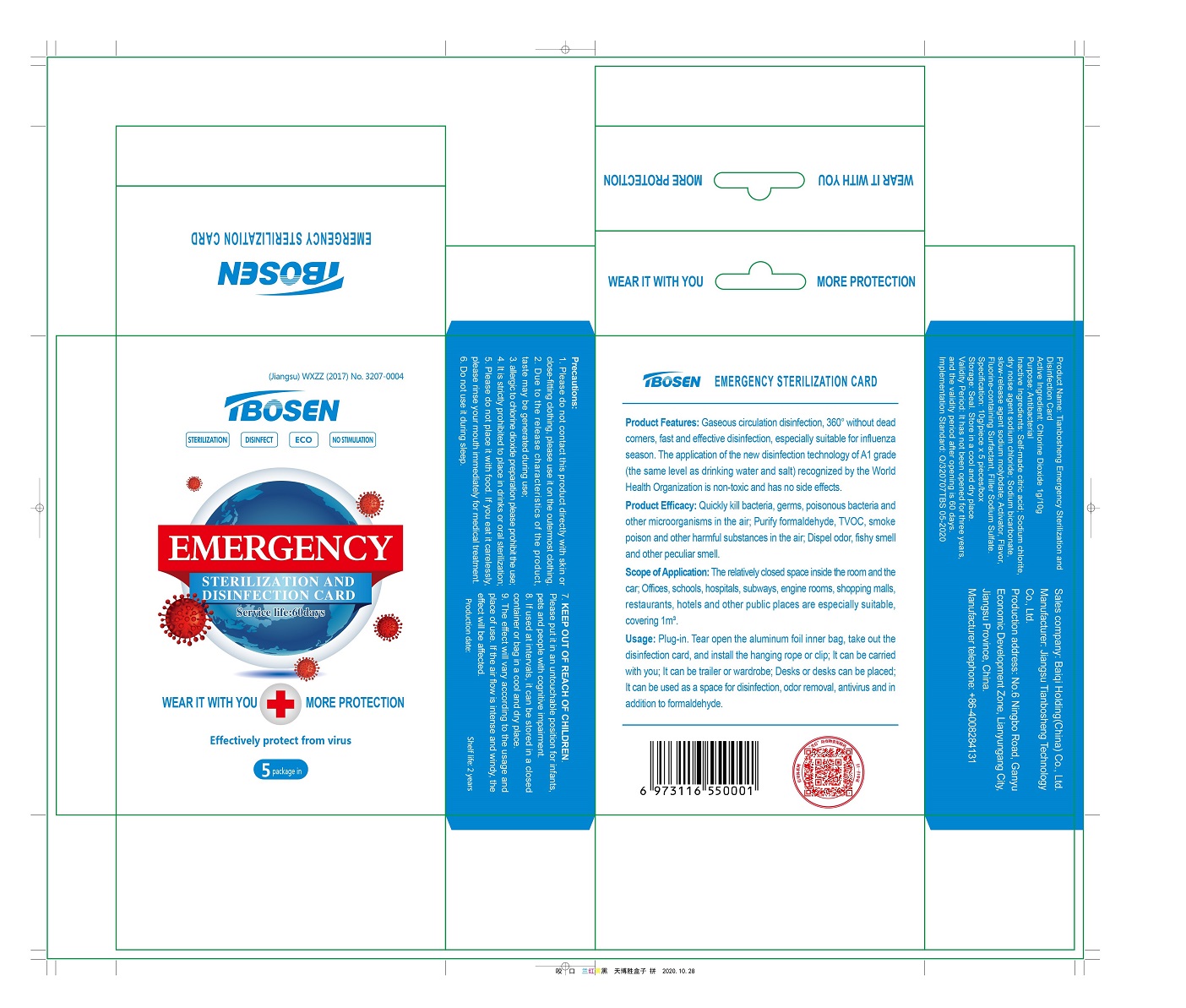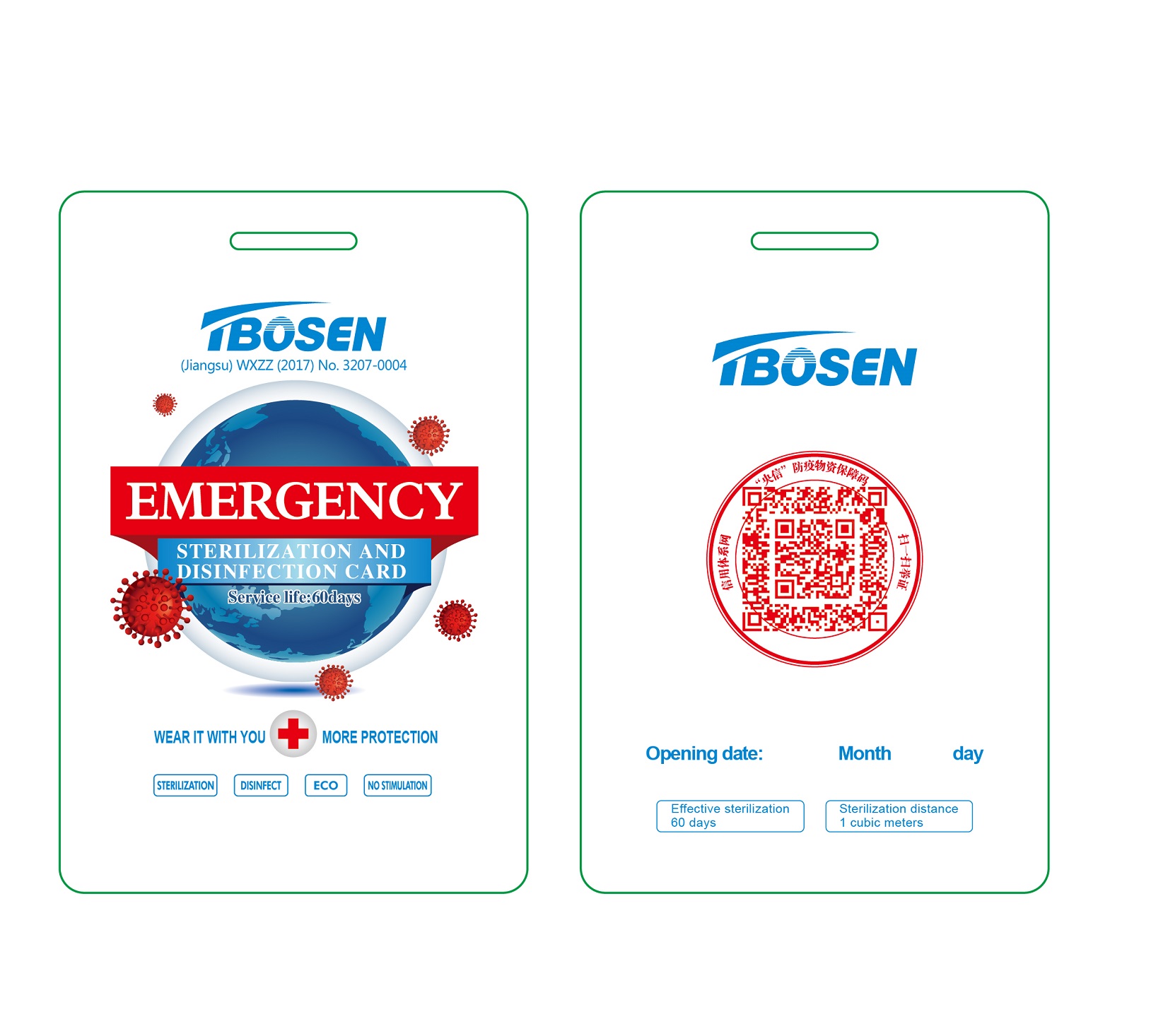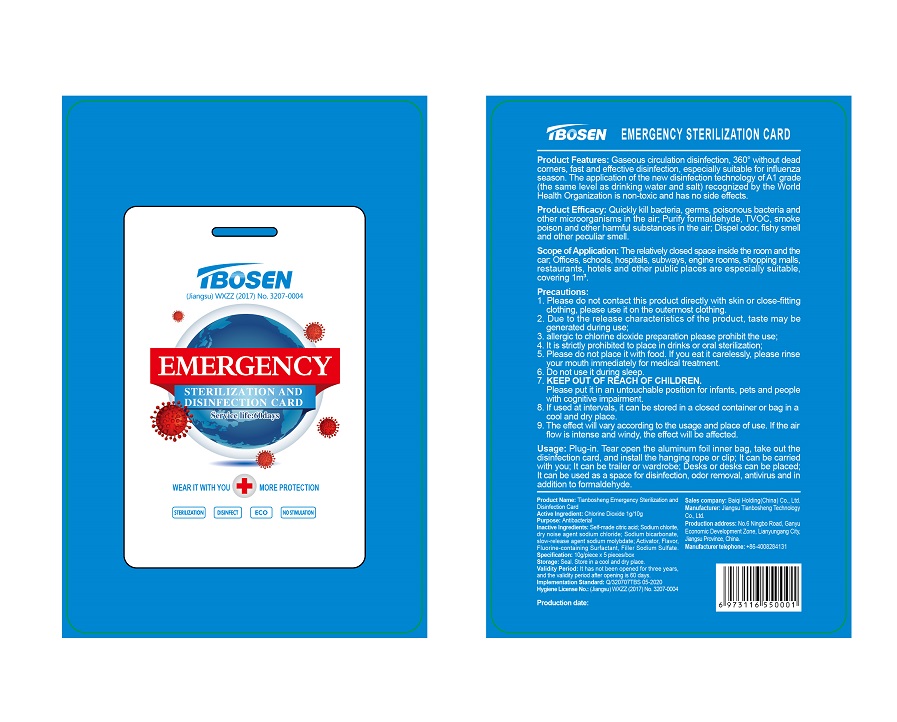 DRUG LABEL: TBOSEN EMERGENCY STERILIZATION CARD
NDC: 81130-101 | Form: GRANULE, DELAYED RELEASE
Manufacturer: Jiangsu Tianbosheng Technology Co., Ltd.
Category: otc | Type: HUMAN OTC DRUG LABEL
Date: 20201123

ACTIVE INGREDIENTS: CHLORINE DIOXIDE 1 g/10 g
INACTIVE INGREDIENTS: SODIUM MOLYBDATE 0.5 g/10 g; CITRIC ACID MONOHYDRATE 4 g/10 g; N-ACETYLCAPROLACTAM 0.2 g/10 g; SODIUM CHLORIDE 1.75 g/10 g; SODIUM BICARBONATE 0.5 g/10 g; SODIUM CHLORITE 2 g/10 g; SODIUM SULFATE 0.04 g/10 g; METHYL BENZOATE 0.01 g/10 g

Tbosen Sterilization Card, ClO2, Granules

Active ingredient

Chlorine Dioxide: 1g/pack ...... Purpose: Antibacterial

Inactive ingredients

Citric acid

Sodium chlorite

Sodium chloride

Sodium bicarbonate

Sodium molybdate

Activator

Sodium sulfate

Essence

Purpose

Antibacterial

When using

Please do not contact this product directly with skin or close-fitting clothing, please use it on the outermost clothing.

Please do not place it with food. If you eat it carelessly, please rinse your mouth immediately for medical treatment.

Do not use it during sleep.

Do not use

Allergic to chlorine dioxide preparation please prohibit the use.

It is strictly prohibited to place in drinks or oral sterilization.

Stop use

Due to the release characteristics of the product, taste may be generated during use.

If irritation or discomfort occurs, discontinue use and see a doctor.

Ask doctor

If irritation or discomfort occurs, discontinue use and see a doctor.

If you eat it carelessly, please rinse your mouth immediately for medical treatment.

Ask doctor/pharmacist when you current use other drugs.

KEEP OUT OF REACH OF CHILDREN

Please put it in an untouchable position for infants, pets and people with cognitive impairment.

Questions

Please contact us when you have any questions.

Telephone: +86-4008284131

Pregnancy or breast feeding

Pregnant or breast feeding women shall follow doctor advice.

Indications & usage

Product Features; Gaseous circulation disinfection, 360° without dead corners, fast and effective disinfection, especially suitable for influenza season. The application of the new disinfection technology of A1 grade (the same level as drinking water and salt) recognized by the World Health Organization is non-toxic and has no side effects.

Product Efficacy: Quickly kill bacteria, germs, poisonous bacteria and other microorganisms in the air; Purify formaldehyde, TVOC, smoke poison and other harmful substances in the air; Dispel odor, fishy smell and other peculiar smell.

Usage: Plug-in. Tear open the aluminum foil inner bag, take out the disinfection card, and install the hanging rope or clip; It can be carried with you; It can be trailer or wardrobe; Desks or desks can be placed; It can be used as a space for disinfection, odor removal, antivirus and in addition to formaldehyde.

Dosage & administration

10g/piece * 5 pieces/box

Scope of Application: The relatively closed space inside the room and the car; Offices, schools, hospitals, subways, engine rooms, shopping malls, restaurants, hotels and other public places are especially suitable, covering 1m³.

Dosage forms & strengths

Dosage form: Release Granules.

Strength: 1g/10g.

Warnings

Precautions:

1. Please do not contact this product directly with skin or close-fitting clothing, please use it on the outermost clothing.

2. Allergic to chlorine dioxide preparation please prohibit the use.

3. It is strictly prohibited to place in drinks or oral sterilization.

4. Please do not place it with food. If you eat it carelessly, please rinse your mouth immediately for medical treatment.

5. Do not use it during sleep.

6. Please put it in an untouchable position for infants, pets and people with cognitive impairment.

Other Information

1. Storage: Seal. Store in a cool and dry place.
2. Validity Period: It has not been opened for three years, and the validity period after opening is 60 days.
3. If used at intervals, it can be stored in a closed container or bag in a cool and dry place.
4. Due to the release characteristics of the product, taste may be generated during use.
5. The effect will vary according to the usage and place of use. If the air flow is intense and windy, the effect will be affected.